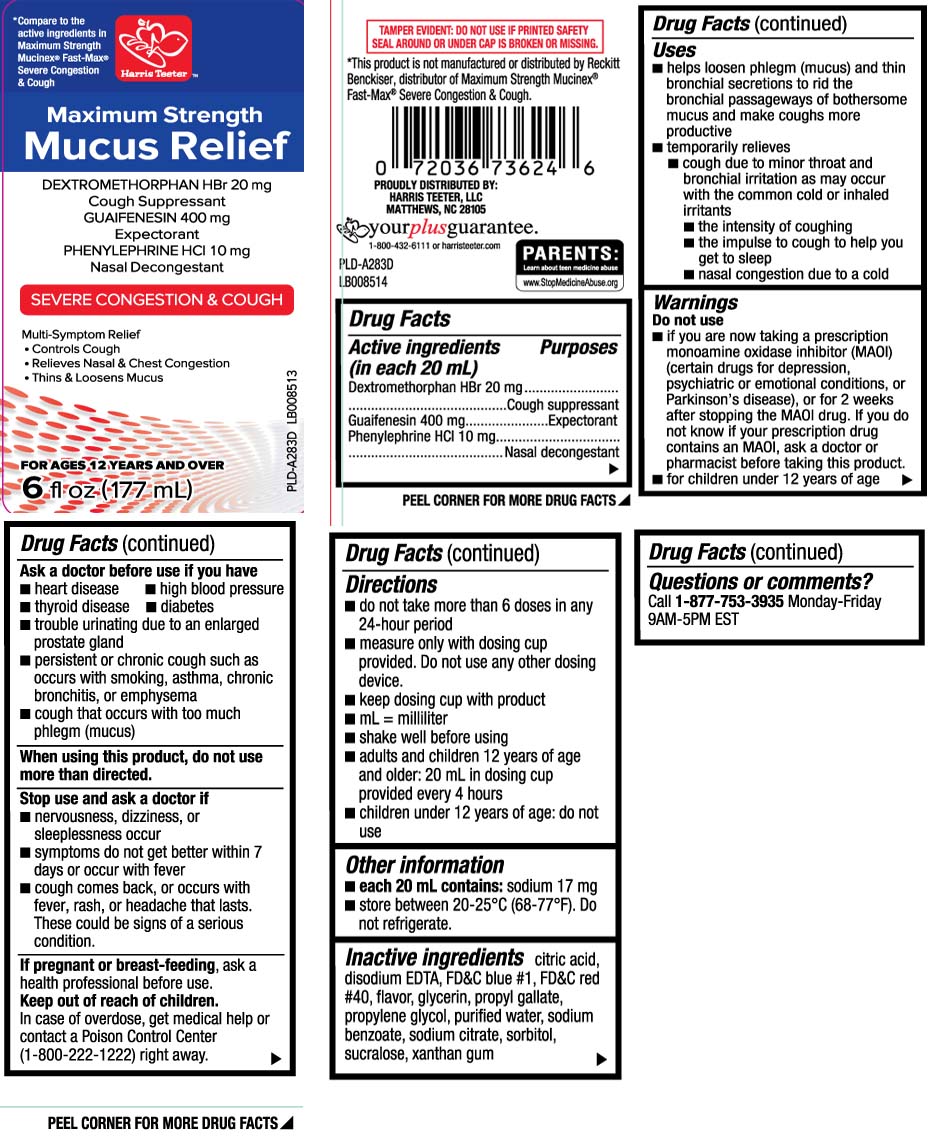 DRUG LABEL: Mucus Relief Severe Congestion and Cough
NDC: 69256-337 | Form: LIQUID
Manufacturer: Harris Teeter, LLC
Category: otc | Type: HUMAN OTC DRUG LABEL
Date: 20251216

ACTIVE INGREDIENTS: DEXTROMETHORPHAN HYDROBROMIDE 20 mg/20 mL; GUAIFENESIN 400 mg/20 mL; PHENYLEPHRINE HYDROCHLORIDE 10 mg/20 mL
INACTIVE INGREDIENTS: ANHYDROUS CITRIC ACID; EDETATE DISODIUM; FD&C BLUE NO. 1; FD&C RED NO. 40; GLYCERIN; PROPYL GALLATE; PROPYLENE GLYCOL; WATER; SODIUM BENZOATE; TRISODIUM CITRATE DIHYDRATE; SORBITOL; SUCRALOSE; XANTHAN GUM

Drug Facts

Active ingredients (in each 20 mL)

Dextromethorphan HBr 20 mg

Guaifenesin 400 mg

Phenylephrine HCl 10 mg

Purposes

Cough suppressant

Expectorant

Nasal decongestant

Uses

- helps loosen phlegm (mucus) and thin bronchial secretions to rid the bronchial passageways of bothersome mucus and make coughs more productive
- temporarily relieves:
  - cough due to minor throat and bronchial irritation as may occur with the common cold or inhaled irritants
  - the intensity of coughing
  - the impulse to cough to help you get to sleep
  - nasal congestion due to a cold

Warnings

Do not use

- if you are now taking a prescription monoamine oxidase inhibitor (MAOI) (certain drugs for depression, psychiatric or emotional conditions, or Parkinson's disease), or for 2 weeks after stopping the MAOI drug. If you do not know if your prescription drug contains an MAOI, ask a doctor or pharmacist before taking this product.
- for children under 12 years of age

Ask a doctor before use if you have

- heart disease
- high blood pressure
- thyroid disease
- diabetes
- trouble urinating due to an enlarged prostate gland
- persistent or chronic cough such as occurs with smoking, asthma, chronic bronchitis, or emphysema
- cough that occurs with too much phlegm (mucus)

When using this product

do not use more than directed.

Stop use and ask a doctor if

- nervousness, dizziness or sleeplessness occur
- symptoms do not get better within 7 days or occur with fever
- cough comes back, or occurs with fever, rash or headache that lasts.

These could be signs of a serious condition.

If pregnant or breast-feeding,

ask a health professional before use.

Keep out of reach of children.

In case of overdose, get medical help or contact a Poison Control Center (1-800-222-1222) right away.

Directions

- do not take more than 6 doses in a 24-hour period
- measure only with dosing cup provided. Do not use any other dosing device.
- keep dosing cup with product
- mL=milliliter
- shake well before using
- adults and children 12 years of age and older: 20 mL in dosing cup provided every 4 hours
- children under 12 years of age: do not use

Other information

- each 20 mL contains: sodium 17 mg
- store between 20-25ºC (68-77ºF). Do not refrigerate.

Inactive ingredients

citric acid, disodium EDTA, FD&C blue #1, FD&C red #40, flavor, glycerin, propyl gallate, propylene glycol, purified water, sodium benzoate, sodium citrate, sorbitol, sucralose, xanthan gum

Questions or comments?

Call 1-877-753-3935 Monday-Friday 9AM-5PM EST

Principal Display Panel

*Compare to the active ingredients in Maximum Strength Mucinex® Fast-Max® Severe Congestion & Cough

Maximum Strength

Mucus Relief

DEXTROMETHORPHAN HBr 20 mg

Cough Suppressant

GUAIFENESIN 400 mg

Expectorant

PHENYLEPHRINE HCl 10 mg

Nasal Decongestant

SEVERE CONGESTION & COUGH

Multi-Symptom Relief

- Controls Cough
- Relieves Nasal & Chest Congestion
- Thin & Loosen Mucus

FOR AGES 12 YEARS AND OVER

FL OZ (mL)

TAMPER EVIDENT: DO NOT USE IF PRINTED SAFETY SEAL AROUND OR UNDER CAP IS BROKEN OR MISSING.

*This product is not manufactured or distributed by Reckitt Benckiser, distributor of Maximum Strength Mucinex® Fast-Max® Severe Congestion & Cough.

PROUDLY DISTRIBUTED BY:

HARRIS TEETER, LLC

MATTHEWS, NC 28105

Package Label

HARRIS TEETER Maximum Strength Mucus Relief Severe Congestion & Cough